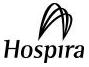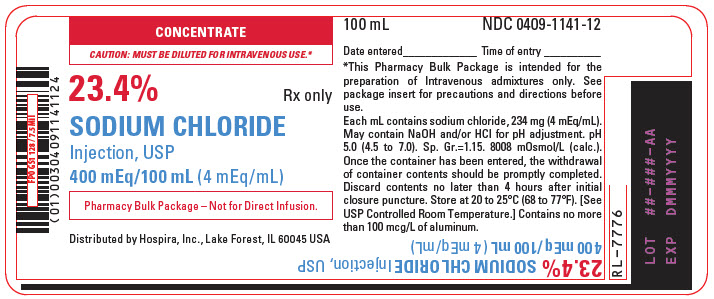 DRUG LABEL: SODIUM CHLORIDE
NDC: 0409-1141 | Form: INJECTION, SOLUTION, CONCENTRATE
Manufacturer: Hospira, Inc.
Category: prescription | Type: HUMAN PRESCRIPTION DRUG LABEL
Date: 20251111

ACTIVE INGREDIENTS: SODIUM CHLORIDE 234 mg/1 mL
INACTIVE INGREDIENTS: SODIUM HYDROXIDE; HYDROCHLORIC ACID; WATER

23.4%
Sodium Chloride Injection, USP
400 mEq (4 mEq/mL)
Additive Solution

CONCENTRATE

CAUTION: MUST BE DILUTED FOR I.V. USE.

Concentrated Solution - For use only after dilution with compatible intravenous fluids to correct sodium deficiency when oral replacement is not feasible.

Glass Fliptop Vials

Rx only

Pharmacy Bulk Package –
Not for Direct Infusion

DESCRIPTION

23.4% Sodium Chloride Injection, USP Additive Solution is a sterile, nonpyrogenic, concentrated solution for intravenous administration ONLY AFTER DILUTION to replenish electrolytes. The preparations contain 23.4 g of sodium chloride (400 mEq each of Na+ and Cl^-) in Water for Injection, USP.

The solution contains no bacteriostat, antimicrobial agent or added buffer. The additive may contain sodium hydroxide and/or hydrochloric acid for pH adjustment. The pH is 5.0 (4.5 to 7.0). The specific gravity is 1.15, and the osmolarity is 8008 mOsmol/L (calc).

Sodium Chloride, USP is chemically designated NaCl, a white crystalline compound freely soluble in water. The molecular weight is 58.44 g/mol.

The Pharmacy Bulk Package is a sterile dosage form which contains multiple single doses for preparation of admixtures for intravenous infusion (see DOSAGE AND ADMINISTRATION).

CLINICAL PHARMACOLOGY

Sodium chloride in water dissociates to provide sodium (Na^+) and chloride (Cl^-) ions. These ions are normal constituents of the body fluids (principally extracellular) and are essential for maintaining electrolyte balance.

Sodium is the principal cation of extracellular fluid. It comprises more than 90% of the total cations at its normal plasma concentration of approximately 142 mEq/L. While the sodium ion can diffuse across cell membranes, the intracellular sodium is maintained at a much lower concentration than extracellular sodium through the expenditure of energy by the cell (so called "sodium cation pump"). Loss of intracellular potassium ion is usually accompanied by an increase in intracellular sodium ion. Sodium is the principal ion that determines osmotic pressure of interstitial fluids and the degree of tissue hydration.

When serum sodium concentration is low, the secretion of antidiuretic hormone (ADH) by the pituitary is inhibited, thereby preventing water reabsorption by the distal renal tubules. On the other hand, adrenal secretion of aldosterone increases renal tubular reabsorption of sodium in an effort to re-establish normal serum sodium concentration.

Chloride (Cl^-) has an integral role in buffering action when oxygen and carbon dioxide exchange occurs in the red blood cells.

The distribution and excretion of sodium (Na^+) and chloride (Cl^-) are largely under the control of the kidney which maintains a balance between intake and output.

INDICATIONS AND USAGE

23.4% Sodium Chloride Injection, USP is indicated for use as an electrolyte replenisher in parenteral fluid therapy. It serves as an additive for total parenteral nutrition (TPN) and as an additive for carbohydrate containing I.V. fluids.

CONTRAINDICATIONS

23.4% Sodium Chloride Injection, USP Additive Solution is contraindicated in patients with hypernatremia or fluid retention.

WARNINGS

23.4% Sodium Chloride Injection, USP is hypertonic and must be diluted prior to administration. Inadvertent direct injection or absorption of concentrated sodium chloride solution may give rise to sudden hypernatremia and such complications as cardiovascular shock, central nervous system disorders, specifically osmotic demyelination syndrome, extensive hemolysis, cortical necrosis of the kidneys and severe local tissue necrosis (if administered extravascularly).

Solutions containing sodium ions should be used with great care, if at all, in patients with congestive heart failure, severe renal insufficiency and in clinical states in which there exists edema with sodium retention.

In patients with diminished renal function, administration of solutions containing sodium may result in sodium retention. The intravenous administration of this solution (after appropriate dilution) can cause fluid and/or solute overloading resulting in dilution of other serum electrolyte concentrations, overhydration, congested states or pulmonary edema.

Excessive administration of potassium-free solutions may result in significant hypokalemia.

WARNING: This product contains aluminum that may be toxic. Aluminum may reach toxic levels with prolonged parenteral administration if kidney function is impaired. Premature neonates are particularly at risk because their kidneys are immature, and they require large amounts of calcium and phosphate solutions, which contain aluminum.

Research indicates that patients with impaired kidney function, including premature neonates, who receive parenteral levels of aluminum at greater than 4 to 5 mcg/kg/day accumulate aluminum at levels associated with central nervous system and bone toxicity. Tissue loading may occur at even lower rates of administration.

PRECAUTIONS

General

Excessive amounts of sodium chloride by any route may cause hypokalemia and acidosis. Excessive amounts by the parenteral route may precipitate congestive heart failure and acute pulmonary edema, especially in patients with cardiovascular disease and in patients receiving corticosteroids or corticotropin or drugs that may give rise to sodium retention. Special caution should be used in administering sodium-containing solutions to patients with severe renal impairment, cirrhosis of the liver or other edematous or sodium-retaining states.

Clinical evaluation and periodic laboratory determinations are necessary to monitor changes in fluid balance, electrolyte concentrations, and acid-base balance during prolonged parenteral therapy or whenever the condition of the patient warrants such evaluation. Do not use unless the solution is clear and seal is intact.

Pregnancy

Animal reproduction studies have not been conducted with 23.4% Sodium Chloride Injection, USP. It is also not known whether sodium chloride can cause fetal harm when administered to a pregnant woman or can affect reproduction capacity. Sodium chloride should be given to a pregnant woman only if clearly needed.

Nursing Mothers

It is not known whether 23.4% Sodium Chloride Injection, USP is excreted in human milk. Because many drugs are excreted in human milk, caution should be exercised when sodium chloride is administered to a nursing woman.

Pediatric Use

Safety and effectiveness of 23.4% Sodium Chloride Injection, USP have not been established in pediatric patients. Its limited use in pediatric patients has been inadequate to fully define proper dosage and limitations for use.

Geriatric Use

An evaluation of current literature revealed no clinical experience identifying differences in response between elderly and younger patients. In general, dose selection for an elderly patient should be cautious, usually starting at the low end of the dosing range, reflecting the greater frequency of decreased hepatic, renal, or cardiac function, and of concomitant disease or other drug therapy.

This drug is known to be substantially excreted by the kidney, and the risk of toxic reactions to this drug may be greater in patients with impaired renal function. Because elderly patients are more likely to have decreased renal function, care should be taken in dose selection, and it may be useful to monitor renal function.

ADVERSE REACTIONS

Sodium overload can occur with intravenous infusion of excessive amounts of sodium-containing solutions. See WARNINGS and PRECAUTIONS.

OVERDOSAGE

Excessive administration of 23.4% Sodium Chloride Injection, USP may result in electrolyte imbalance with water retention, edema, loss of potassium and aggravation of an existing acidosis. See WARNINGS.

DOSAGE AND ADMINISTRATION

23.4% Sodium Chloride Injection, USP Additive Solution is administered intravenously only after addition to a larger volume of fluid.

The dose, dilution and rate of injection are dependent upon the individual needs of each patient. In solutions for total parenteral nutrition (TPN), 120 mEq of sodium/day (range: 75–180 mEq/day) is the recommended adult dosage, whereas the recommended dosage is 3–4 mEq/kg/day for preterm infants.

Parenteral drug products should be inspected visually for particulate matter and discoloration prior to administration, whenever solution and container permit. Discard unused portion.

Additives may be incompatible with the fluid dispensed from this container. Consult with pharmacist, if available. When admixing, use aseptic technique, mix thoroughly and do not store.

Directions for Proper Use of Pharmacy Bulk Package

Use Aseptic Technique

1. For hanger application, peel off the paper liner from both ends of the tape hanger to expose 3/4 in. long adhesive portions. Adhere each end to the label on the bottle.
2. During use, container must be stored and all manipulations performed in an appropriate laminar flow hood.
3. Remove cover from container and cleanse closure with antiseptic.
4. Insert suitable sterile dispensing set or transfer device and suspend unit in a laminar flow hood. The closure should be entered only once and after initial entry, the withdrawal of container contents should be completed promptly in one continuous operation. Should this not be possible, a maximum time of 4 hours from initial closure puncture is permitted to complete fluid transfer operations; i.e., discard container no later than 4 hours after initial closure puncture.
5. Sequentially dispense aliquots of 23.4% Sodium Chloride Injection, USP into intravenous containers using appropriate transfer device. During fluid transfer operations, the Pharmacy Bulk Package should be maintained under the storage conditions recommended in the labeling.
6. Inspect solution after admixing. Discard if the solution is discolored or particulates are observed.

HOW SUPPLIED

23.4% Sodium Chloride Injection, USP (4 mEq/mL) is supplied as follows:

NDC No | Type Container | Dose / Volume | Concentration
0409-1141-02 | Pharmacy Bulk Package – Glass Fliptop Vial | 400 mEq/100 mL | 4 mEq/mL

STORAGE AND HANDLING

Store at 20 to 25°C (68 to 77°F). [See USP Controlled Room Temperature].

Distributed by Hospira, Inc., Lake Forest, IL 60045 USA

LAB-1106-3.0

Revised: 11/2025

PRINCIPAL DISPLAY PANEL - 100 mL Vial Label

CONCENTRATE

CAUTION: MUST BE DILUTED FOR INTRAVENOUS USE.*

23.4%
SODIUM CHLORIDE
Injection, USP
400 mEq/100 mL (4 mEq/mL)

Rx only

Pharmacy Bulk Package – Not for Direct Infusion.

Distributed by Hospira, Inc., Lake Forest, IL 60045 USA